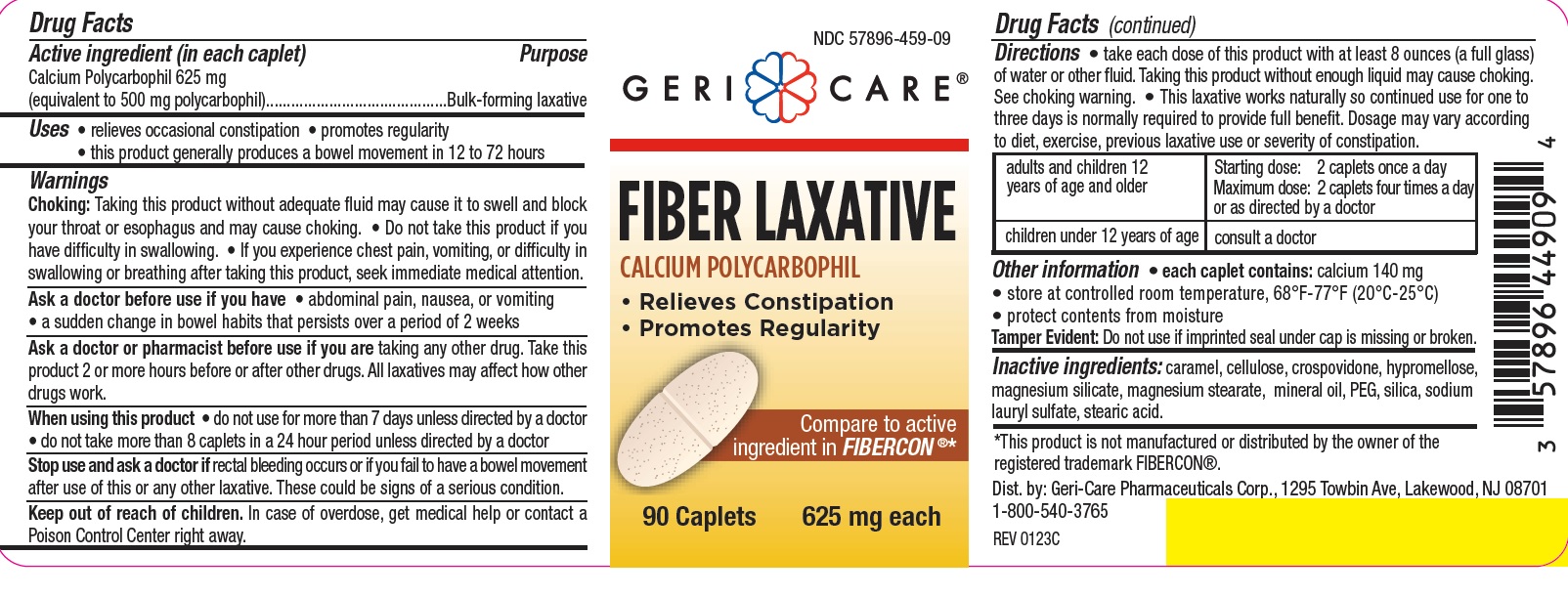 DRUG LABEL: Fiber Laxative
NDC: 57896-459 | Form: TABLET, FILM COATED
Manufacturer: Geri-Care Pharmaceutical Corp
Category: otc | Type: HUMAN OTC DRUG LABEL
Date: 20250407

ACTIVE INGREDIENTS: CALCIUM POLYCARBOPHIL 625 mg/1 1
INACTIVE INGREDIENTS: LIGHT MINERAL OIL; STEARIC ACID; CROSPOVIDONE; MAGNESIUM SILICATE; MAGNESIUM STEARATE; HYPROMELLOSES; CELLULOSE, MICROCRYSTALLINE; POLYETHYLENE GLYCOL 400; SILICON DIOXIDE; CARAMEL; SODIUM LAURYL SULFATE

gc 449(459)

Active ingredient (in each caplet)

Calcium Polycarbophil 625 mg

(equivalent to 500 mg polycarbophil)

Purpose

Bulk-forming laxative

Uses

- relieves occasional constipation
- promotes regularity
- this product generally produces a bowel movement in 12 to 72 hours

Warnings

Choking: Taking this product without adequate fluid may cause it to swell and block your throat or esophagus and may cause choking.

• Do not take this product if you have difficulty in swallowing.

• If you experience chest pain, vomiting, or difficulty in swallowing or breathing after taking this product, seek immediate medical attention.

Ask a doctor before use if you have

• abdominal pain, nausea, or vomiting

• a sudden change in bowel habits that persists over a period of 2 weeks.

Ask a doctor or pharmacist before use if you are taking any other drug. Take this
product 2 or more hours before or after other drugs. All laxatives may affect how other
drugs work.

When using this product

- do not use for more than 7 days unless directed by a doctor
- do not take more than 8 caplets in a 24 hour period unless directed by a doctor

Stop use and ask a doctor if rectal bleeding occurs or if you fail to have a bowel movement
after use of this or any other laxative. These could be signs of a serious condition.

Keep out of reach of children. In case of overdose, get medical help or contact a Poison Control Center right away.

Directions

- take each dose of this product with at least 8 ounces (a full glass) of water or other fluid. Taking this product without enough liquid may cause choking. See choking warning.
- This laxative works naturally so continued use for one to three days is normally required to provide full benefit. Dosage may vary according to diet, exercise, previous laxative use or severity of constipation.

adults and children 12 years of age and older | Starting dose: 2 caplets once a day Maximum dose: 2 caplets four times a day or as directed by a doctor
children under 12 years of age | consult a doctor

Other information

• each caplet contains: calcium 140 mg

• store at controlled room temperature, 68°F-77°F (20°C-25°C)

• protect contents from moisture

Tamper Evident: Do not use if imprinted seal under cap is missing or broken.

Inactive ingredients

caramel, cellulose, crospovidone, hypromellose,
magnesium silicate, magnesium stearate, mineral oil, PEG, silica, sodium
lauryl sulfate, stearic acid